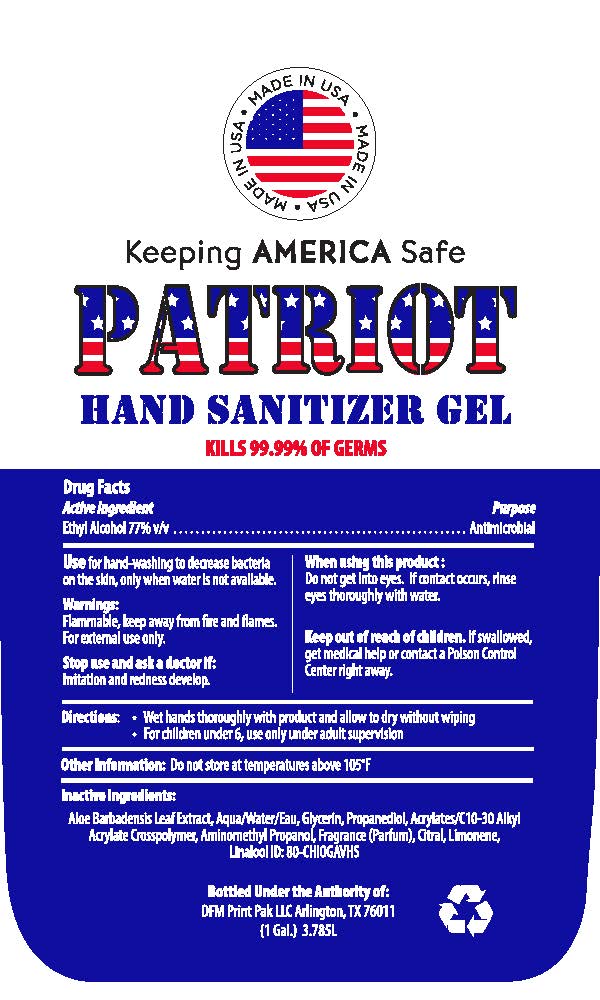 DRUG LABEL: Patriot Hand Sanitizer Gallon
NDC: 75795-499 | Form: GEL
Manufacturer: DFMPRINTPAK3709
Category: otc | Type: HUMAN OTC DRUG LABEL
Date: 20200604

ACTIVE INGREDIENTS: ALCOHOL 2914.76 mL/3785.4 mL
INACTIVE INGREDIENTS: WATER 773.17 mL/3785.4 mL; ALOE VERA LEAF 37.85 mL/3785.4 mL; GLYCERIN 59.62 mL/3785.4 mL

Inactive Ingredients

Inactive Ingredeints for this product are:

Glycerin

Aloe Barbadensis Leaf Extract

Keep Product out of reach of children.

Indications and Use for this product:

Wet hands thoroughly with product and allow to dry without wiping.

OTC Purpose

Purpose of this product is to use for hand washing to decrease bacteria

on the skin only when water is unavailable.

Dosage and Administration Section

Dosage is a small amount of gel into palm of hands,

to be rubbed into hands.

Warnings Section

Do not ingest product, for external use only.

Flammable, keep away from fire and flames,

See attached product label

Patriot Sanitizer Label FINAL ART.jpg

Active Ingredient is Ethyl Alcohol 77%

Hand Sanitizer Active Ingredient

Ethyl Alcohol 77%